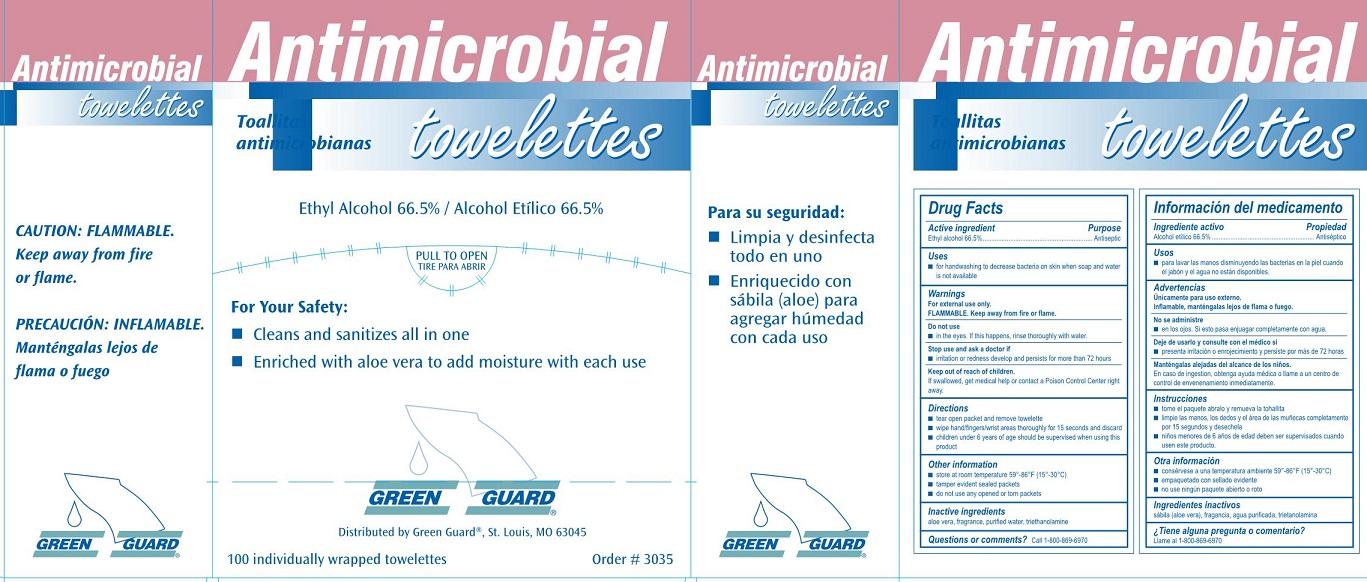 DRUG LABEL: Green Guard Antimicrobial Towelettes
NDC: 47682-350 | Form: LIQUID
Manufacturer: Unifirst First Aid Corporation
Category: otc | Type: HUMAN OTC DRUG LABEL
Date: 20250908

ACTIVE INGREDIENTS: ALCOHOL 665 mL/1 L
INACTIVE INGREDIENTS: WATER; TROLAMINE; ALOE

Green Guard Antimicrobial Towelettes

Active ingredient

Ethyl alcohol 66.5%

Purpose

Antiseptic

Uses

- for handwashing to decrease bacteria on skin when soap and water is not available

Warnings

For external use only.

FLAMMABLE. Keep away from fire or flame.

Do not use

- in the eyes. If this happens, rinse thoroughly with water.

Stop use and ask a doctor if

- irritation or redness develop and persists for more than 72 hours

Keep out of reach of children.

Children under 6 ears of age should be supervised when using this product.

Directions

- tear open packet and remove towellette
- wipe hand/fingers/wrist areas thoroughly for 15 seconds and discard

Other information

- store at room temperature 59º-86ºF (15º-30ºC)
- tamper evident sealed packets
- do not use any opened or torn packets

Inactive ingredients

aloe vera, fragrance, purified water, triethanolamine

Question or comments?

1-800-869-6970

Green Guard Antimicrobial Towellettes Label

Antimicrobial

towellettes

Toallitas antimicrobianas

Ethyl Alcohol 66.5% / Alcohol Etilico 66.5%

Pull To Opem

Tire Para Abrir

For Your Safety:

- Cleans and sanitizes all in one
- Enriched with aloe vera to add moisture with each use

GREEN GUARD®

Distributed by Green Guard®, Si. Louis, MO 63045

100 individually wrapped towellettes

Order # 3035